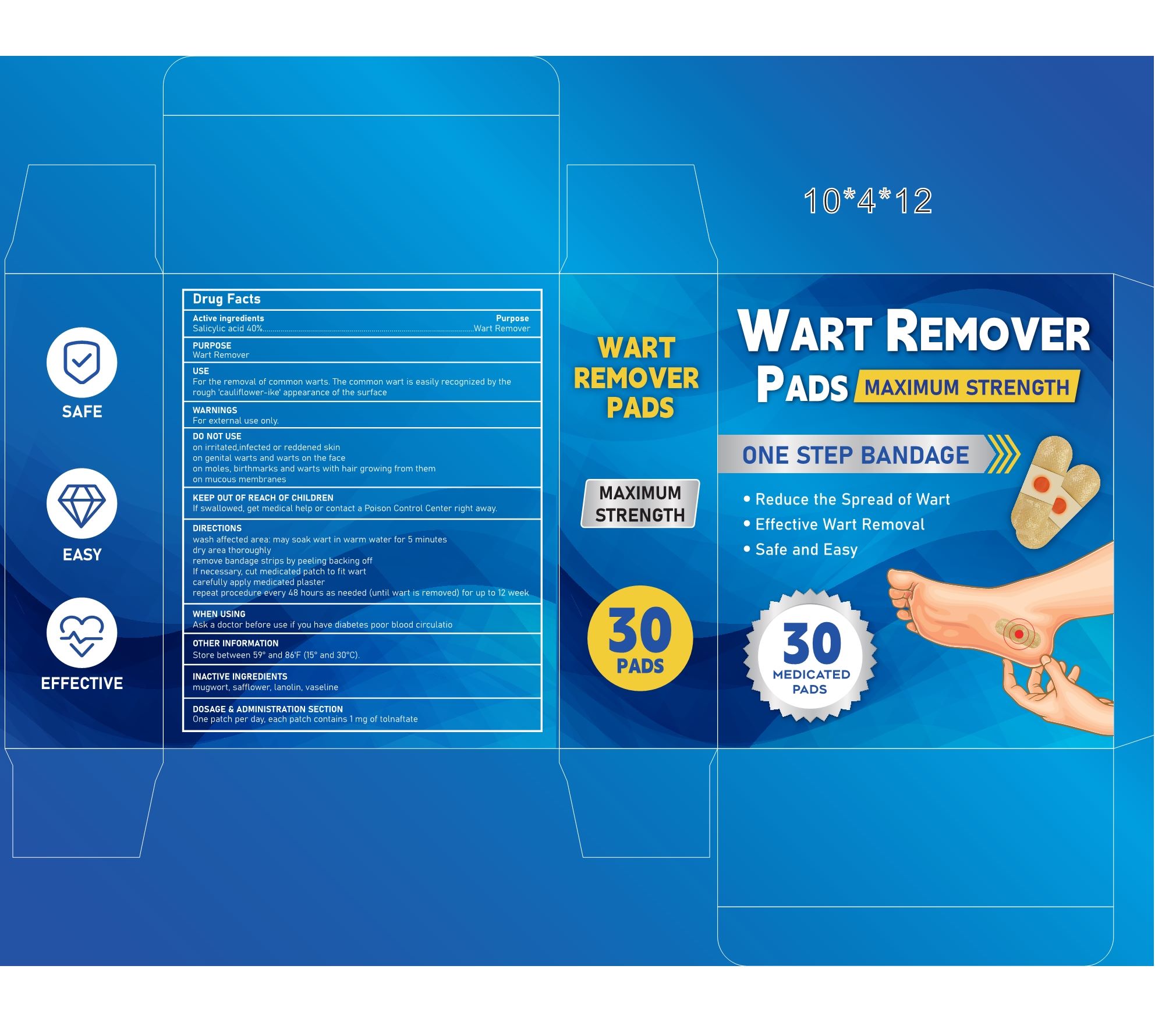 DRUG LABEL: Wart Remover Pads
NDC: 84023-112 | Form: PATCH
Manufacturer: Shenzhen Yangan Technology Co., Ltd.
Category: otc | Type: HUMAN OTC DRUG LABEL
Date: 20240927

ACTIVE INGREDIENTS: SALICYLIC ACID 40 mg/100 mg
INACTIVE INGREDIENTS: SAFFLOWER; PETROLATUM; ARTEMISIA PRINCEPS LEAF; LANOLIN

Wart Remover Pads

ACTIVE INGREDIENT

Salicylic acid 40%

PURPOSE

Wart Remover

For the removal of common warts. The common wart is easily recognized by the rough 'cauliflower-ike' appearance of the surface

DIRECTIONS

wash affected area: may soak wart in warm water for 5 minutes

dry area thoroughly

remove bandage strips by peeling backing off

If necessary, cut medicated patch to fit wart

carefully apply medicated plaster

repeat procedure every 48 hours as needed (until wart is removed) for up to 12 week

Ask a doctor before use if you have diabetes poor blood circulation

WARNINGS

For external use only.

DO NOT USE

on irritated, infected or reddened skin

on genital warts and warts on the face

on moles, birthmarks and warts with hair growing from them on mucous membranes

KEEP OUT OF REACH OF CHILDREN

ASK DOCTOR

If swallowed, get medical help or contact a Poison Control Center right away.

OTHER SAFETY INFORMATION

Store between 59°and 86'F (15°and 30°C).

DOSAGE AND ADMINISTRATION

One patch per day, each patch contains 1 mg of tolnaftate

INACTIVE INGREDIENT

mugwort, safflower, lanolin, vaseline